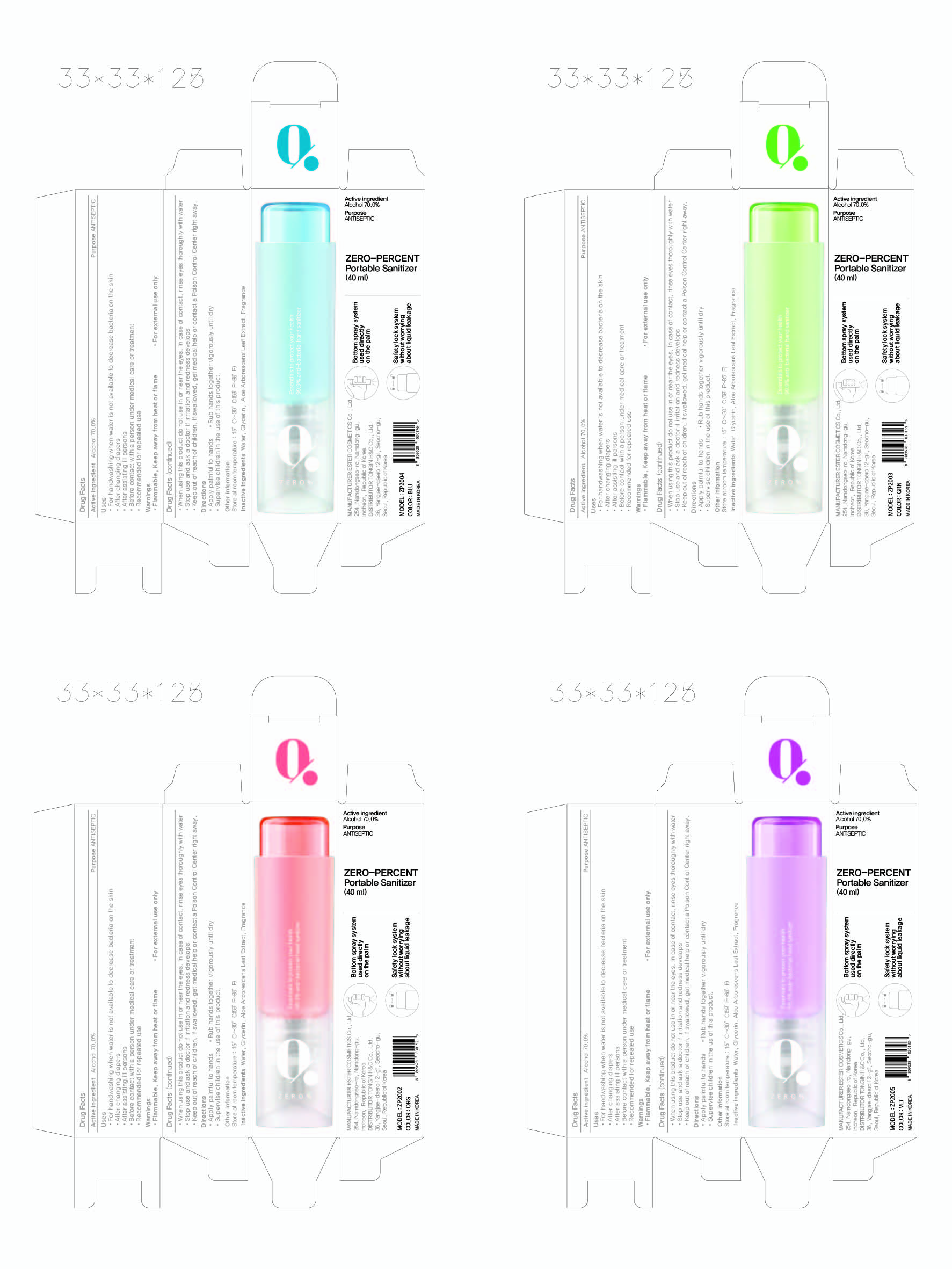 DRUG LABEL: ZERO-PERCENT Portable Sanitizer
NDC: 74004-045 | Form: SPRAY
Manufacturer: Ester Co., Ltd.
Category: otc | Type: HUMAN OTC DRUG LABEL
Date: 20201006

ACTIVE INGREDIENTS: ALCOHOL 28 mL/40 mL
INACTIVE INGREDIENTS: WATER; GLYCERIN; ALOE ARBORESCENS LEAF

[5] ZERO-PERCENT Portable Sanitizer (Fragrance)
74004-045-02
4 colors